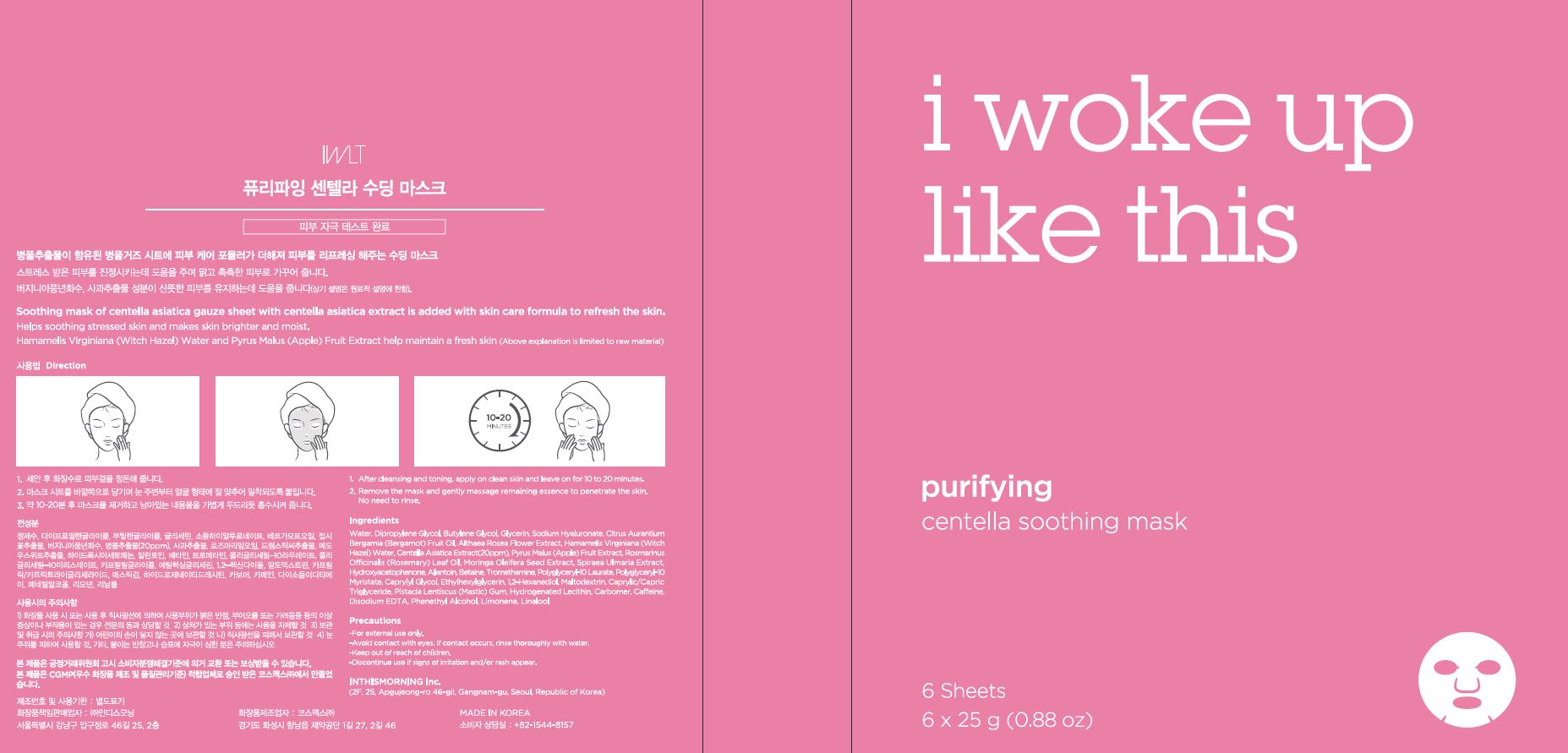 DRUG LABEL: Purifying centella soothing mask
NDC: 71217-0053 | Form: LIQUID
Manufacturer: inthismorning co ltd
Category: otc | Type: HUMAN OTC DRUG LABEL
Date: 20230130

ACTIVE INGREDIENTS: LIMONENE, (+)- 0.00371146 g/100 g; LINALOOL, (+/-)- 0.00109203 g/100 g
INACTIVE INGREDIENTS: WATER; GLYCERIN

Drug Facts

ACTIVE INGREDIENT

limonene, linalool

INACTIVE INGREDIENT

Water+A11:A42
Dipropylene Glycol
Butylene Glycol
Glycerin
Hydroxyacetophenone
Carbomer
Allantoin
Betaine
Caffeine
Tromethamine
Polyglyceryl-10 Laurate
Polyglyceryl-10 Myristate
Caprylyl Glycol
Ethylhexylglycerin
1,2-Hexanediol
Disodium EDTA
Sodium Hyaluronate
Althaea Rosea Flower Extract
Hamamelis Virginiana (Witch Hazel) Water
Citrus Aurantium Bergamia (Bergamot) Fruit Oil
Centella Asiatica Extract
Pyrus Malus (Apple) Fruit Extract
Rosmarinus Officinalis (Rosemary) Leaf Oil
Maltodextrin
Moringa Oleifera Seed Extract
Caprylic/Capric Triglyceride
Pistacia Lentiscus (Mastic) Gum
Hydrogenated Lecithin
Spiraea Ulmaria Extract
Phenethyl Alcohol

PURPOSE

helps soothing stressed skin and makes skin brighter and moist

keep out or reach of the children

INDICATIONS AND USAGE

1 after cleansing and toning, apply on clean skin and leave on for 10 to 20 minutes

2 remove the mask and gently massage remaining essence to penetrate the skin. no need to rinse

WARNINGS

This product is for exeternal use only. Do not use for internal use
Storage and handling precautions
If possible, avoid direct sunlight and store in cool and area of low humidity in order to maintain the quality of the product and avoid misuse
Avoid placing the product near fire and store out in reach of children

- consult a physician in case of abnormal symptoms, such as red spots, swelling or itching, or side effects in the areas of application due to direct light during or after using the product

- do not use on wounded area

DOSAGE AND ADMINISTRATION

for external use only